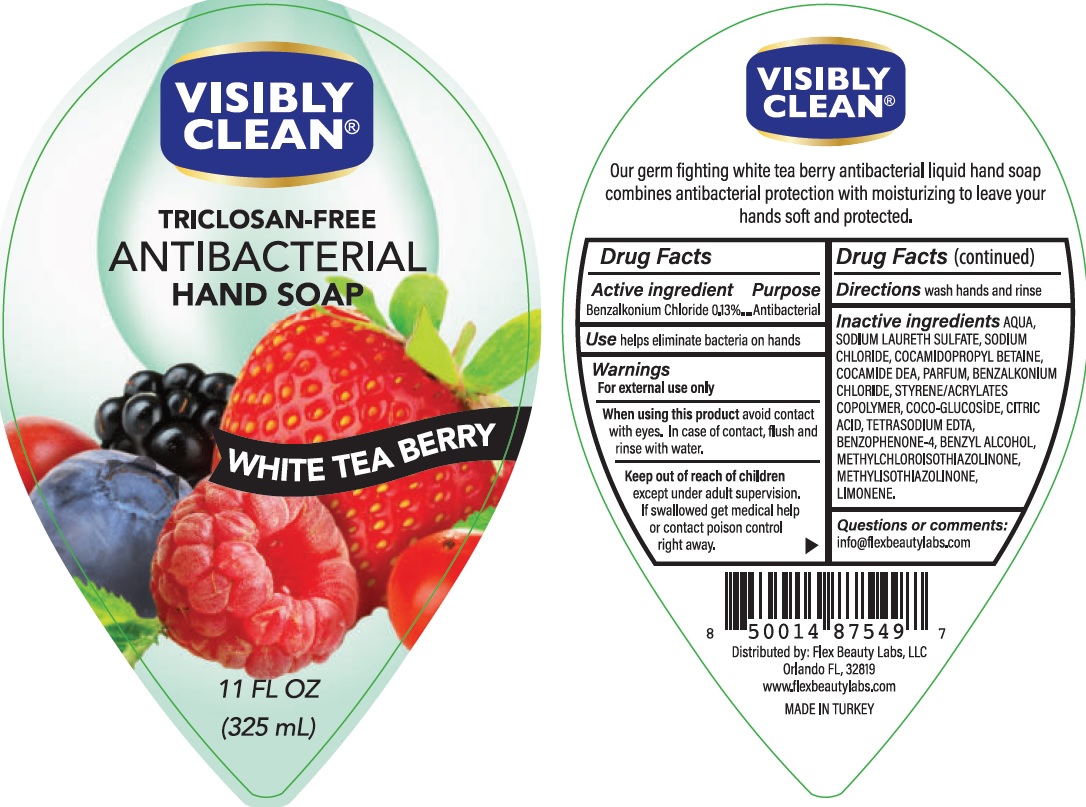 DRUG LABEL: Antibacterial
NDC: 78242-002 | Form: LIQUID
Manufacturer: DIAMO KOZMETIK SANAYI IC VE DIS TICARET LIMITED SIRKETI	
Category: otc | Type: HUMAN OTC DRUG LABEL
Date: 20200622

ACTIVE INGREDIENTS: BENZALKONIUM CHLORIDE 1.3 mg/1 mL
INACTIVE INGREDIENTS: WATER; SODIUM LAURETH SULFATE; COCAMIDOPROPYL BETAINE; COCO DIETHANOLAMIDE; SODIUM CHLORIDE; GLYCERIN; DITETRACYCLINE TETRASODIUM EDETATE; METHYLCHLOROISOTHIAZOLINONE; METHYLISOTHIAZOLINONE; SULISOBENZONE; BENZYL ALCOHOL; ANHYDROUS CITRIC ACID; LIMONENE DIEPOXIDE

Antibacterial, Triclosan free- Visibly Clean Hand Soap- White Tea Berry

ACTIVE INGREDIENT

Benzalkonium Chloride - 0.13%

Purpose - Antibacterial

INDICATIONS AND USAGE

Use help eliminate bacteria on hands

Warnings

For external use only

Stop use and ask a doctor if irritation or redness develops

When using this product

Avoid contact with eyes.In case of contact, flush and rinse with water.

Keep out of reach of children

Except under adult supervision. DO NOT EAT DRINK.

Keep away from food,drink and animal feeding stuffs,

If swallowed get medical help or contact posion control right away.

Directions

Wash hands and rinse

INACTIVE INGREDIENT

Water, Sodium Laureth Sulfate, Cocamidopropyl Betaine, Sodium Chloride, Citric Acid, Glycerin, Fragrance, Tetrasodium EDTA, Methylchloroisothiazolinone, Methylisothiazolinone, Benzophenone-4,Benzyl Alcohol,Limonene.